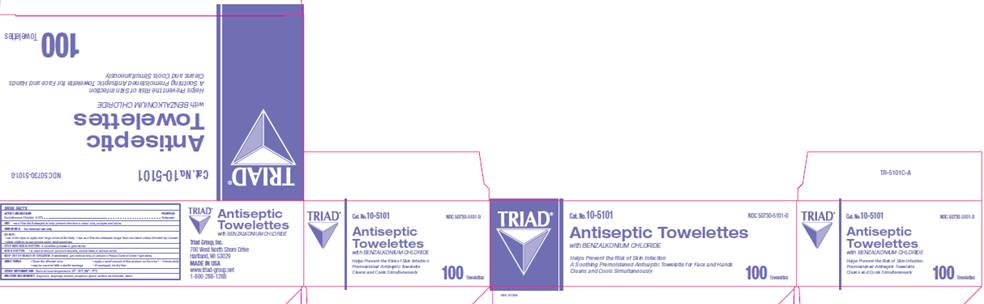 DRUG LABEL: BZK Antiseptic Towelette
NDC: 50730-5101 | Form: SOLUTION
Manufacturer: H and P Industries, Inc. dba Triad Group
Category: otc | Type: HUMAN OTC DRUG LABEL
Date: 20091201

ACTIVE INGREDIENTS: benzalkonium chloride .0013 mL/1 1
INACTIVE INGREDIENTS: isopropyl alcohol; propylene glycol; sodium bicarbonate; water

DRUG FACTS

ACTIVE INGREDIENT

Benzalkonium chloride .13% w/v

PURPOSE

Antiseptic

USE

First aid antiseptic to help prevent the risk of infection in minor cuts, scrapes and burns

WARNINGS

For external use only.

Do not

- use in the eyes
- apply over large areas of the body
- allow children to use except under adult supervision

Ask a doctor in case of

- deep or puncture wounds
- animal bites
- serious burns

Stop use and ask a doctor

if condition persists or gets worse

Keep out of reach of children

If swallowed, get medical help or contact a Poison Control Center right away.

DIRECTIONS

- clean the affected area
- apply a small amount of this product to the area 1-3 times daily
- may be covered with a sterile bandage
- if bandaged, let dry first

INACTIVE INGREDIENTS

fragrance, isopropyl alcohol, propylene glycol, sodium bicarbonate, water

CARTON INFORMATION

TRIAD
Cat. No. 10-5101
NDC 50730-5101-0
ANTISEPTIC
TOWELETTES
with BENZALKONIUM CHLORIDE
A Soothing Pre-Moistened Antiseptic Towelette for Face and Hands
Cleans and Cools Simultaneously
100 towelettes